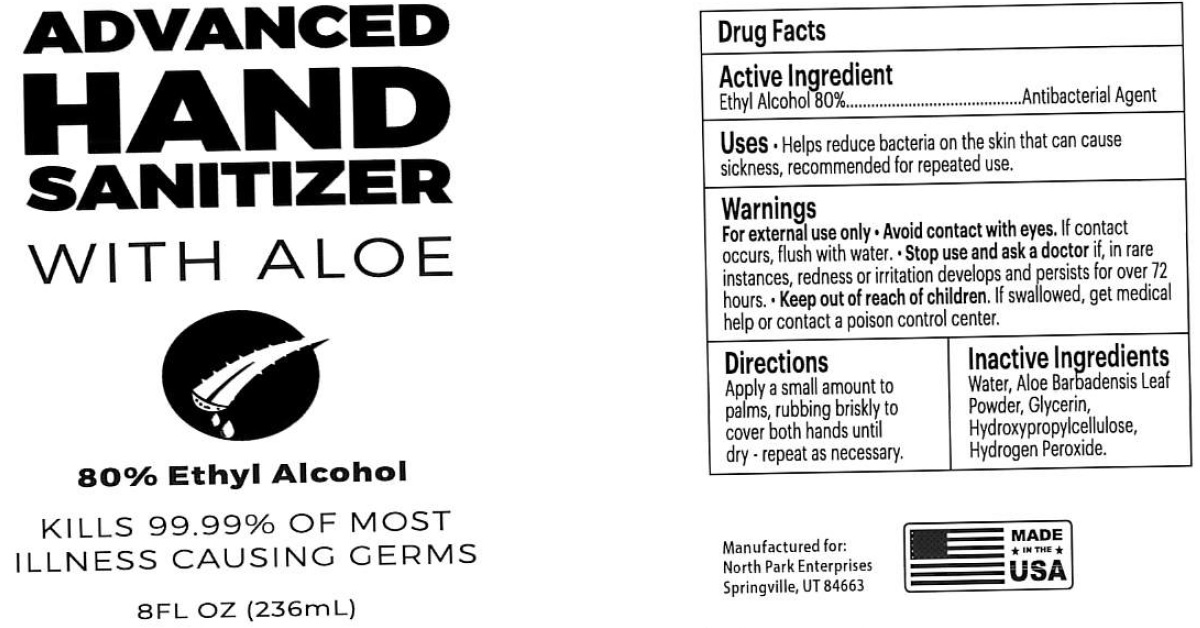 DRUG LABEL: Advanced Hand Sanitizer with Aloe bottles
NDC: 77650-080 | Form: GEL
Manufacturer: North Park Enterprises, LC
Category: otc | Type: HUMAN OTC DRUG LABEL
Date: 20200615

ACTIVE INGREDIENTS: ALCOHOL 0.8 1/1 mL
INACTIVE INGREDIENTS: WATER; ALOE VERA LEAF; GLYCERIN; HYDROXYPROPYL CELLULOSE, UNSPECIFIED; HYDROGEN PEROXIDE

Advanced Hand Sanitizer with Aloe bottles

Active Ingredient

Ethyl Alcohol 80%

PURPOSE

Antibacterial Agent

Uses.

Helps reduce bacteria on the skin that can cause sickness, recommended for repeated use.

Warnings

For external use only

- Avoid contact with eyes.If contact occurs, flush with water.

Stop use and ask a doctor

if, in rare instances, redness or irritation develops and persists for over 72 hours

Keep out of reach of children.

If swallowed, get medical help or contact a poison control center.

Directions

Apply a small amount to palms, rubbing briskly to cover both hands until dry-repeat as necessary.

Inactive Ingredients

Water, Aloe Barbadensis Leaf Powder, Glycerin, Hydroxypropylcellulose, Hydrogen Peroxide.